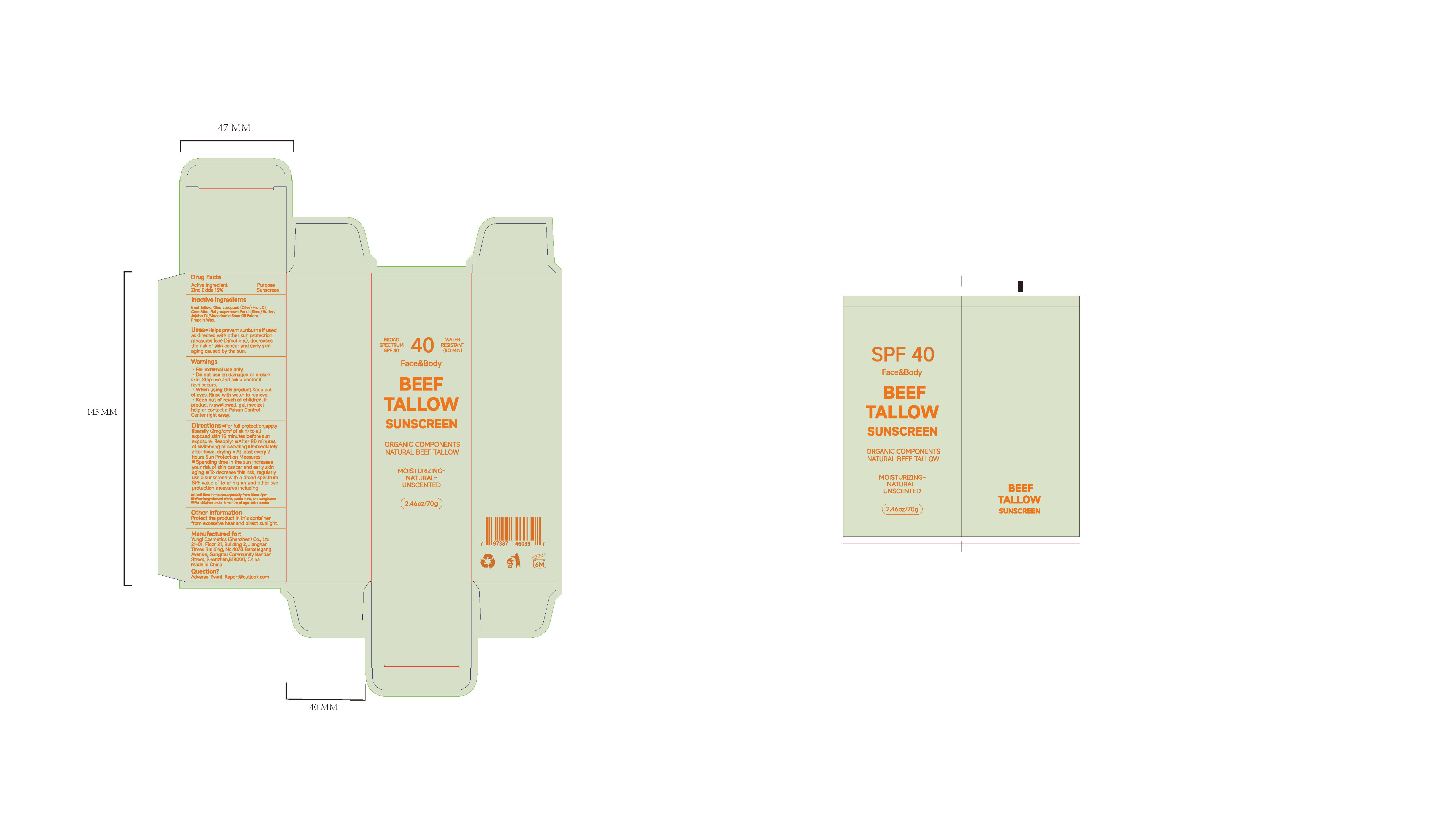 DRUG LABEL: BEEF TALLOW SUNSCREEN
NDC: 84763-004 | Form: CREAM
Manufacturer: Yunqi Cosmetics (Shenzhen) Co., Ltd
Category: otc | Type: HUMAN OTC DRUG LABEL
Date: 20250424

ACTIVE INGREDIENTS: ZINC OXIDE 0.13 g/1 g
INACTIVE INGREDIENTS: OLEA EUROPAEA (OLIVE) FRUIT OIL; BUTYROSPERMUM PARKII (SHEA) BUTTER; BEEF TALLOW; WHITE WAX; JOJOBA OIL, RANDOMIZED; PROPOLIS WAX

BEEF TALLOW SUNSCREEN

ACTIVE INGREDIENT

Zinc Oxide

PURPOSE

Sunscreen

INDICATIONS AND USAGE

Uses.Halps prevent sunburnm lf usedas directed with oter sun protectionmeasures (see Directions)decreasesthe risk of skin cancer and early skinaging caused by the sun.

WARNINGS

For exteral use onby

Do not use on damaged or brokenskin. Stop use and ask a doctor if rash occurs

WHEN USING

When using thls preduct keep outof eves. Rinse with water to remove.

Stop use and ask a doctor if rash occurs.

KEEP OUT OF REACH OF CHILDREN

keep out or reach of chlldren. lfproduct is swallowed, get medicalhelp ar contact a Poison ContolCenter night away

DOSAGE AND ADMINISTRATION

Directions .For full protection,applyliberally(2mg/cm of skin) to allexposed skin 15 minutes before sunexposure.Reapply:After 80 minutesof swlmming or sweating.lmmedlatelyafter towel drying .At least every 2hours Sun Protection Measures:Spending time in the sun increasesyour risk of skin cancer and early skinaging .To decrease this risk, regularlyuse a sunscreen with a broad spectumSPF value of 15 or higher and cther sunprotection measures including
Lmit tma In the sun,especlally tom 10em 2pm

Wesr lon aleeved chirtss, pants, hats, and runglaeses

For chilcren under b manths of aoet aek a cloctor

INACTIVE INGREDIENT

Beef Tallow
Olea Europaea (Olive)Fruit Oil
Cera Alba
Butyrospermum Parkii (Shea) Butter
Jojoba Oil/Macadamia Seed Oil Esters
Propolis Wax